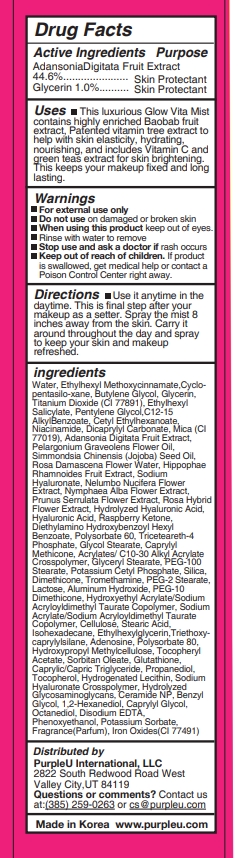 DRUG LABEL: PurpleU GLOW ULTIMATE VITA MIST
NDC: 90069-204 | Form: LIQUID
Manufacturer: Purple U Co., Ltd
Category: otc | Type: HUMAN OTC DRUG LABEL
Date: 20200902

ACTIVE INGREDIENTS: GLYCERIN 1 g/100 mL; ADANSONIA DIGITATA FRUIT 44.6 g/100 mL
INACTIVE INGREDIENTS: PRUNUS MUME FRUIT; PANTHENOL; ALCOHOL; POVIDONE, UNSPECIFIED; ALCEA ROSEA FLOWER; ROSA X DAMASCENA FLOWER OIL; CENTELLA ASIATICA WHOLE; CHAMOMILE; HYALURONIC ACID; SODIUM CITRATE; CITRIC ACID MONOHYDRATE; ASCORBIC ACID; ROSEMARY; HYALURONATE SODIUM; PURSLANE; JASMINUM OFFICINALE FLOWER; PENTYLENE GLYCOL; 1,2-HEXANEDIOL; OCTYLDODECETH-16; MEDIUM-CHAIN TRIGLYCERIDES; PROPANEDIOL; CERAMIDE 3; CAPRYLYL GLYCOL; SODIUM ACETYLATED HYALURONATE; PHENOXYETHANOL; MELISSA OFFICINALIS LEAF; HYDROGENATED SOYBEAN LECITHIN; HYDROLYZED GLYCOSAMINOGLYCANS (BOVINE; 50000 MW); WATER; BERGAMOT OIL; NELUMBO NUCIFERA FLOWER; ROSA CANINA SEED; POLYOXYL 60 HYDROGENATED CASTOR OIL; BUTYLENE GLYCOL; ETHYLHEXYLGLYCERIN; HAMAMELIS VIRGINIANA TOP WATER; MATRICARIA CHAMOMILLA WHOLE; TANACETUM PARTHENIUM WHOLE; NYMPHAEA ALBA FLOWER; GREEN TEA LEAF; DENDRANTHEMA INDICUM FLOWER; THYME; HIPPOPHAE RHAMNOIDES FRUIT; PRUNUS SERRULATA FLOWER; EDETATE DISODIUM ANHYDROUS; ETHYLENE GLYCOL MONOBENZYL ETHER; POTASSIUM SORBATE

90069-204

Active Ingredients

Adansonia Digitata Fruit Extract 44.6%

Glycerin 1.0%

Purpose

Skin Protectant

Uses

This luxurious Glow Vita Mist contains highly enriched Baobab fruit extract, Patented vitamin tree extract to help with skin elasticity, hydrating, nourishing, and includes Vitamin C and green teas extract for skin brightening. This keeps your makeup fixed and long lasting.

Warnings

- For external use only
- Do not use on damaged or broken skin
- When using this product keep out of eyes. Rinse with water to remove

Stop use and ask a doctor if

rash occurs

Keep out of reach of children.

If product is swallowed, get medical help or contact a Poison Control Center right away.

Directions

Use it anytime in the daytime. This is final step after your makeup as a setter. Spray the mist 8 inches away from the skin. Carry it around throughout the day and spray to keep your skin and makeup refreshed.

ingredients

Water, Ethylhexyl Methoxycinnamate,Cyclo- pentasilo-xane, Butylene Glycol, Glycerin, Titanium Dioxide (CI 77891), Ethylhexyl Salicylate, Pentylene Glycol,C12-15 AlkylBenzoate, Cetyl Ethylhexanoate, Niacinamide, Dicaprylyl Carbonate, Mica (CI 77019), Adansonia Digitata Fruit Extract, Pelargonium Graveolens Flower Oil, Simmondsia Chinensis (Jojoba) Seed Oil, Rosa Damascena Flower Water, Hippophae Rhamnoides Fruit Extract, Sodium Hyaluronate, Nelumbo Nucifera Flower Extract, Nymphaea Alba Flower Extract, Prunus Serrulata Flower Extract, Rosa Hybrid Flower Extract, Hydrolyzed Hyaluronic Acid, Hyaluronic Acid, Raspberry Ketone, Diethylamino Hydroxybenzoyl Hexyl Benzoate, Polysorbate 60, Triceteareth-4 Phosphate, Glycol Stearate, Caprylyl Methicone, Acrylates/ C10-30 Alkyl Acrylate Crosspolymer, Glyceryl Stearate, PEG-100 Stearate, Potassium Cetyl Phosphate, Silica, Dimethicone, Tromethamine, PEG-2 Stearate, Lactose, Aluminum Hydroxide, PEG-10 Dimethicone, Hydroxyethyl Acrylate/Sodium Acryloyldimethyl Taurate Copolymer, Sodium Acrylate/Sodium Acryloyldimethyl Taurate Copolymer, Cellulose, Stearic Acid, Isohexadecane, Ethylhexylglycerin,Triethoxy- caprylylsilane, Adenosine, Polysorbate 80, Hydroxypropyl Methylcellulose, Tocopheryl Acetate, Sorbitan Oleate, Glutathione, Caprylic/Capric Triglyceride, Propanediol, Tocopherol, Hydrogenated Lecithin, Sodium Hyaluronate Crosspolymer, Hydrolyzed Glycosaminoglycans, Ceramide NP, Benzyl Glycol, 1,2-Hexanediol, Caprylyl Glycol, Octanediol, Disodium EDTA, Phenoxyethanol, Potassium Sorbate, Fragrance(Parfum), Iron Oxides(CI 77491)

Package Label

50ml NDC: 90069-204-01 Label